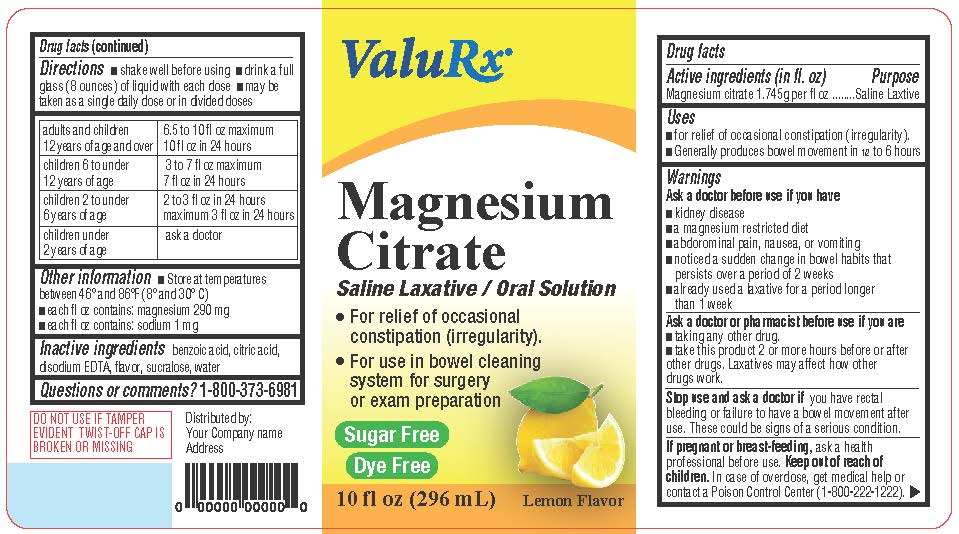 DRUG LABEL: Magnesium Citrate
NDC: 83059-0127 | Form: LIQUID
Manufacturer: Shield Pharmaceuticals Corp
Category: otc | Type: HUMAN OTC DRUG LABEL
Date: 20260126

ACTIVE INGREDIENTS: MAGNESIUM CITRATE 1.745 g/296 mL
INACTIVE INGREDIENTS: BENZOIC ACID; CITRIC ACID; DISODIUM EDTA-COPPER 1.745 g/296 mL; SUCRALOSE; WATER

Magnesium Citrate Oral Solution - Lemon

Active Ingredient

Magnesium citrate 1.745g per fl oz

Purpose

Saline Laxtive

Use

- for relief of occasional constipation (irregularity).
- Generally produces bowel movement in 1/2 to 6 hours

Ask a doctor before use if you have

- kidney disease
- a magnesium restricted diet
- abdorominal pain, nausea, or vomiting
- noticed a sudden change in bowel habits that persists over a period of 2 weeks
- already used a laxative for a period longer than 1 week

Ask a doctor or pharmacist before use if you are

- taking any other drug.
- take this product 2 or more hours before or after other drugs. Laxatives may affect how other drugs work.

Stop use and ask a doctor if you have rectal
bleeding or failure to have a bowel movement after use. These could be signs of a serious condition.

PREGNANCY OR BREAST FEEDING

If pregnant or breast-feeding,ask a health professional before use.

Keep out of reach of children.In case of overdose, get medical help or contact a Poison Control Center (1-800-222-1222).

Directions

- shake well before using _ drink a full glass (8 ounces) of liquid with each dose
- may be taken as a single daily dose or in divided doses

adults and children 12 years of age and over | 6.5 to 10 fl oz maximum 10 fl oz in 24 hours
children 6 to under 3 to 12 years of age | 7 fl oz maximum 7 fl oz in 24 hours
children 2 to under 6 years of age | 2 to 3 fl oz in 24 hours maximum 3 fl oz in 24 hours
children under 2 years of age | ask a doctor

Other Information

- Store at temperatures between 46° and 86°F (8° and 30° C)
- each fl oz contains: magnesium 290 mg
- each fl oz contains: sodium 1 mg

Inactive Ingredients

benzoic acid, citric acid, disodium EDTA, flavor, sucralose, water

Questions?

1-800-373-6981